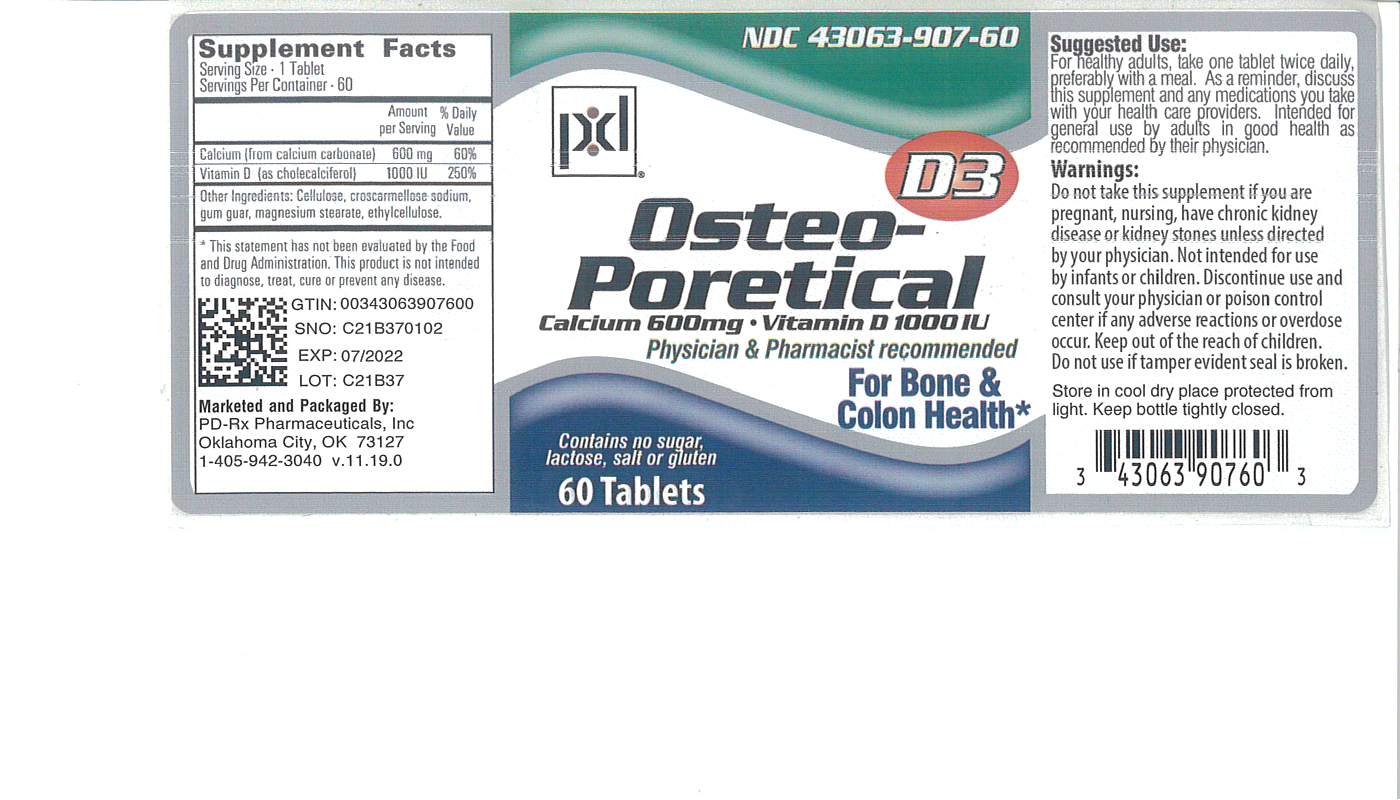 DRUG LABEL: Osteo-Poretical
NDC: 43063-907 | Form: TABLET, FILM COATED
Manufacturer: PD-Rx Pharmaceuticals, Inc.
Category: other | Type: DIETARY SUPPLEMENT
Date: 20210921

ACTIVE INGREDIENTS: CHOLECALCIFEROL 1000 [iU]/1 1; CALCIUM CARBONATE 600 mg/1 1
INACTIVE INGREDIENTS: POWDERED CELLULOSE; CROSCARMELLOSE SODIUM; MAGNESIUM STEARATE; GUAR GUM; ETHYLCELLULOSE, UNSPECIFIED

Supplement Facts

Serving Size 1 Tablet

Servings Per Container 60

 | Amount Per Serving | % Daily Value
Vitamin D (as cholecalciferol) | (1000 IU) | 250%
Calcium (as calcium carbonate) | 600 mg | 60%

Other ingredients: cellulose, croscarmellose sodium, gum guar, magnesium stearate, ethylcellulose.

* This statement has not been evaluated by the Food and Drug Administration. This product is not intended to diagnose, treat, cure or prevent disease.

DOSAGE AND ADMINISTRATION

For healthy adults, take one tablet twice daily, preferably with a meal. As a reminder, discuss this supplement and any medications you take with your health care providers. Intended for general use by adults in good health as recommended by their physician.

WARNINGS

Do not take this supplement if pregnant nursing, have chronic kidney disease or kidney stones unless directed by your physicians. Not intended for use by infants or children. Discontinue use and consult your physician or poison control center if any adverse reactions or overdose occur. Keep out of reach of children. Do not use if tamper evident seal is broken.

SAFE HANDLING WARNING

Store in a cool dry place protected from light.Keep bottle tightly closed.

PACKAGE LABEL

For Bone & Colon Health*

Physician & Pharmacist recommended

Contains no sugar, lactose, salt or gluten

Osteo-Poretical

Calcium Supplement

Calcium 600 mg + 1000 IU Vitamin D